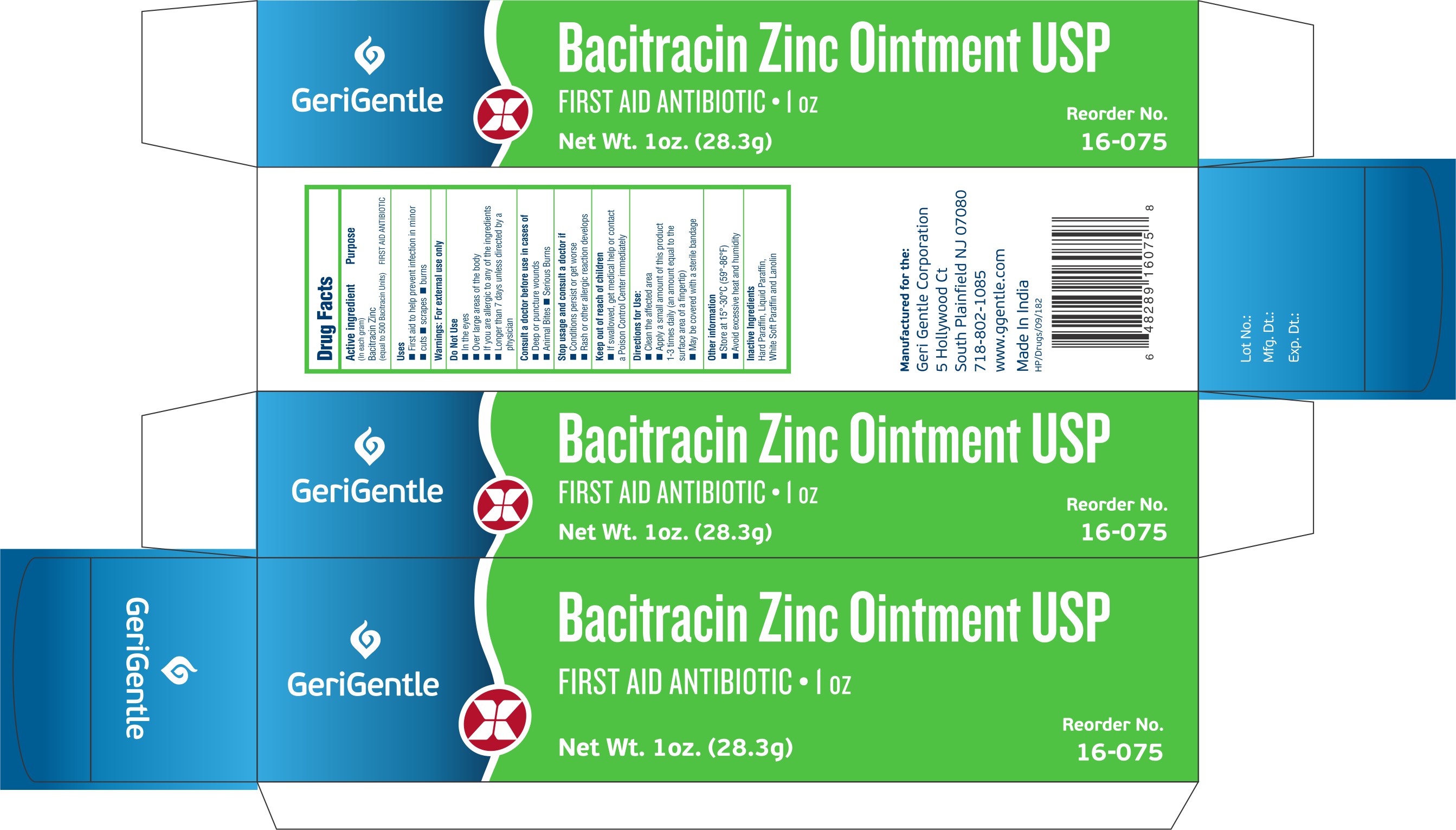 DRUG LABEL: Gerigentle-Bacitracin zinc
NDC: 69771-106 | Form: OINTMENT
Manufacturer: Geri-Gentle Corporation
Category: otc | Type: HUMAN OTC DRUG LABEL
Date: 20251023

ACTIVE INGREDIENTS: BACITRACIN ZINC 500 [USP'U]/1 g
INACTIVE INGREDIENTS: PARAFFIN; MINERAL OIL; WHITE PETROLATUM; LANOLIN

Gerigentle-Bacitracin zinc

Drug Facts

Active ingredient (In each gram)

Bacitracin Zinc (equal to 500 Bacitracin Units)

Purpose

FIRST AID ANTIBIOTIC

Uses

- First aid to help prevent infection in minor
  - cuts
  - scrapes
  - burns

Warnings

For external use only

Do Not Use

- In the eyes
- Over large areas of the body
- If you are allergic to any of the ingredients
- Longer than 7 days unless directed by a physician

Consult a doctor before use in cases of

- Deep or puncture wounds
- Animal Bites
- Serious Burns

Stop usage and consult a doctor if

- Conditions persist or get worse
- Rash or other allergic reaction develops

Keep out of reach of children

- If swallowed, get medical help or contact a Poison Control Center immediately

Directions for Use

- Clean the affected area
- Apply a small amount of this product 1-3 times daily (an amount equal to the surface area of a fingertip)
- May be covered with a sterile bandage

Other information

- Store at 15°-30°C (59°-86°F)
- Avoid excessive heat and humidity

Inactive Ingredients

Hard Paraffin, Liquid Paraffin, White Soft Paraffin and Lanolin